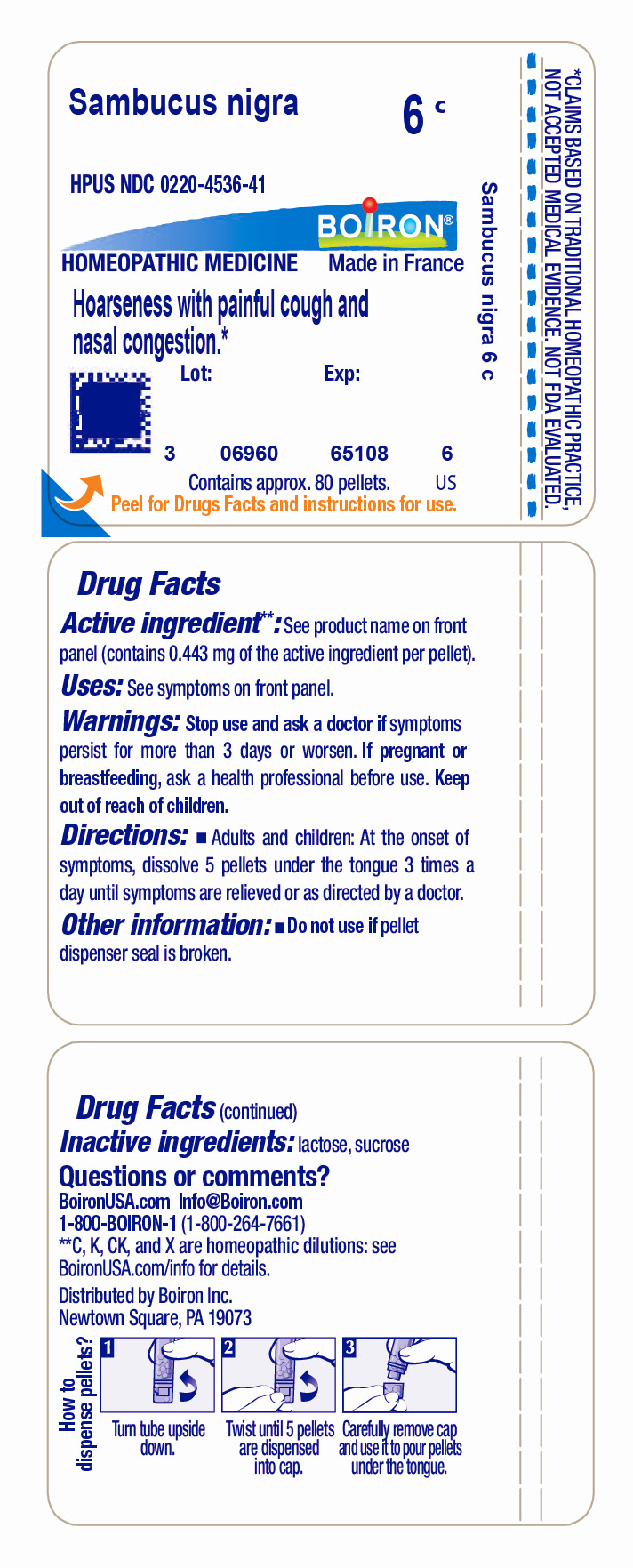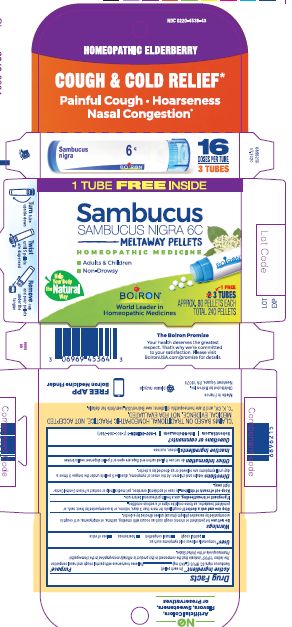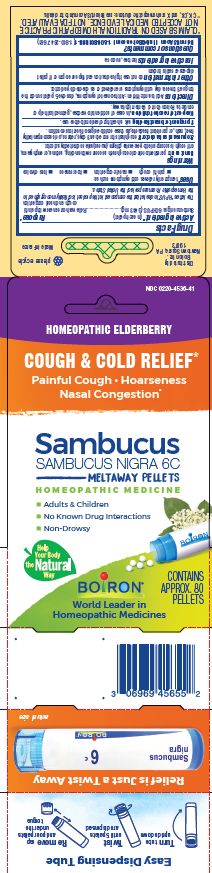 DRUG LABEL: Sambucus nigra
NDC: 0220-4536 | Form: PELLET
Manufacturer: Boiron
Category: homeopathic | Type: HUMAN OTC DRUG LABEL
Date: 20230720

ACTIVE INGREDIENTS: SAMBUCUS NIGRA FLOWERING TOP 6 [hp_C]/6 [hp_C]
INACTIVE INGREDIENTS: SUCROSE; LACTOSE, UNSPECIFIED FORM

Sambucus nigra 6C

ACTIVE INGREDIENT

Tube - Sambucus nigra 6C (**contains 0.443 mg of the active ingredient per pellet)

Box - Sambucus nigra 6C HPUS (**contains 0.443 mg of the active ingredient in each pellet)

The letters "HPUS" indicate that the components in this product are officially monographed in the Homeopathic Pharmacopoeia of the United States.

PURPOSE

Box - Relieves hoarseness with painful cough and nasal congestion*

INDICATIONS AND USAGE

Tube - Hoarseness with painful cough and nasal congestion*

Box - temporarily relieves cold symptoms such as: painful cough, nasal congestion, hoarseness, loss of voice

DO NOT USE

Box - Do not use for persistent or chronic cough such as with smoking, asthma, or emphysema, or if cough is accompanied by excessive phlegm (mucus) unless directed by a doctor.

STOP USE

Tube - Stop use and ask a doctor if symptoms persist for more than 3 days or worsen

Box - Stop use and ask a doctor if cough lasts for more than 3 days, returns, or is accompanied by fever, rash, or persistent headache, as these could be signs of a serious condition.

PREGNANCY OR BREAST FEEDING

Tube - If pregnant or breast-feeding, ask a health professional before use.

Box - If pregnant or breast-feeding, ask a health professional before use.

Tube - Keep out of reach of children.

Box - Keep out of reach of children. In case of accidental overdose, get medical help or contact a Poison Control Center right away.

Tube - Do not use if pellet dispenser seal is broken.
Contains approx 80 pellets.
How to dispense pellets? Turn tube upside down. Twist until 5 pellets are dispensed into cap. Carefully remove the cap and use it to pour pellets under the tongue.
*CLAIMS BASED ON TRADITIONAL HOMEOPATHIC PRACTICE NOT ACCEPTED MEDICAL EVIDENCE. NOT FDA EVALUATED.
*C,K,CK, and X are homeopathic dilutions: see BoironUSA.com/info for details.

Box - Do not use if glued carton end flaps are open or if pellet dispenser seal is broken.

3 Tubes approx 80 pellets 16 Doses per tube Total 240 pellets

How to dispense pellets? Turn tube upside down. Twist until 5 pellets are dispensed. Remove cap and pour pellets under the tongue.

Adults & Children

Non-drowsy

Meltaway Pellets

Cough & Cold Relief*

*CLAIMS BASED ON TRADITIONAL HOMEOPATHIC PRACTICE NOT ACCEPTED MEDICAL EVIDENCE. NOT FDA EVALUATED.
*C,K,CK, and X are homeopathic dilutions: see BoironUSA.com/info for details.

INACTIVE INGREDIENT

Tube - lactose, sucrose

Box - lactose, sucrose

DOSAGE AND ADMINISTRATION

Tube - Adults and children: At the onset of symptoms, dissolve 5 pellets under the tongue 3 times a day until symptoms are relieved or as directed by a doctor.

Box - Adults and children: Adults and children: At the onset of symptoms, dissolve 5 pellets under the tongue 3 times a day until symptoms are relieved or as directed by a doctor.

QUESTIONS

Tube - 1-800-BOIRON-1 (1-800-264-7661),
BoironUSA.com Info@boiron.com
Distributed by Boiron, Inc. Newtown Square, PA 19073

Box - 1-800-BOIRON-1 (1-800-264-7661),
BoironUSA.com Info@boiron.com
Distributed by Boiron, Inc. Newtown Square, PA 19073